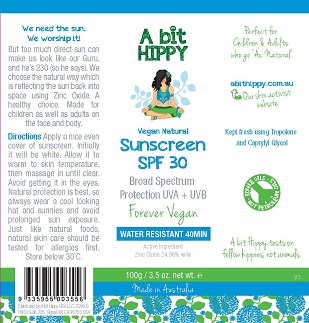 DRUG LABEL: Natural Sunscreen
NDC: 70315-000 | Form: CREAM
Manufacturer: A Bit Hippy
Category: otc | Type: HUMAN OTC DRUG LABEL
Date: 20160512

ACTIVE INGREDIENTS: ZINC OXIDE 24.96 g/100 g
INACTIVE INGREDIENTS: WATER; JOJOBA OIL; GALACTOARABINAN; YELLOW WAX; COCO-CAPRYLATE; SORBITAN OLIVATE; EGG PHOSPHOLIPIDS; POLYGLYCERYL-2 DIPOLYHYDROXYSTEARATE; CETYL PHOSPHATE; POLYGLYCERYL-3 RICINOLEATE; OLEIC ACID; GLYCERIN; TROPOLONE; CAPRYLYL GLYCOL; SODIUM CHLORIDE

Active Ingredient Purpose

Zinc Oxide ............................................... 24.96%

Uses

- helps prevent sunburn
- if used as directed with other sun protection measures (see directions), decreases the risk of skin cancer and early skin aging caused by the sun

Keep out of reach of children.

INDICATIONS AND USAGE

Natural Sunscreen

"Zinc only thanks"

SPF 30

Rubs in Clear

Water Based (Less Greasy)

UVA + UVB Broad Spectrum

For Children & Adults

WATER RESISTANT 40MIN

Active Ingredient

Zinc Oxide 24.96% w/w

DIRECTIONS

Apply a nice even cover of sunscreen.
Initially it will be white.
Allow it to warm to skin temperature, then massage in until clear.
Natural protection is best, so always wear a cool looking hat and sunnies and avoid prolonged sun exposure.
Just like natural foods, natural skin care should be tested for allergies first.

Warnings

- For external use only

- Do not use on damaged or broken skin
- When using this product keep out of eyes. Rinse with water to remove.

- All natural products should be patch tested before use. Stop use if rash occurs.

Inactive Ingredients

water, jojoba oil, galactoarabinan, beeswax, coco caprylate, sorbitan olivate & lecithin & polyglyceryl-2 dipolyhydroxystearate & cetyl phosphate & polyglyceryl-3 polyricinoleate, & oleic acid, glycerin, tropolone, capryl glycol, sodium chloride (salt).

LABEL